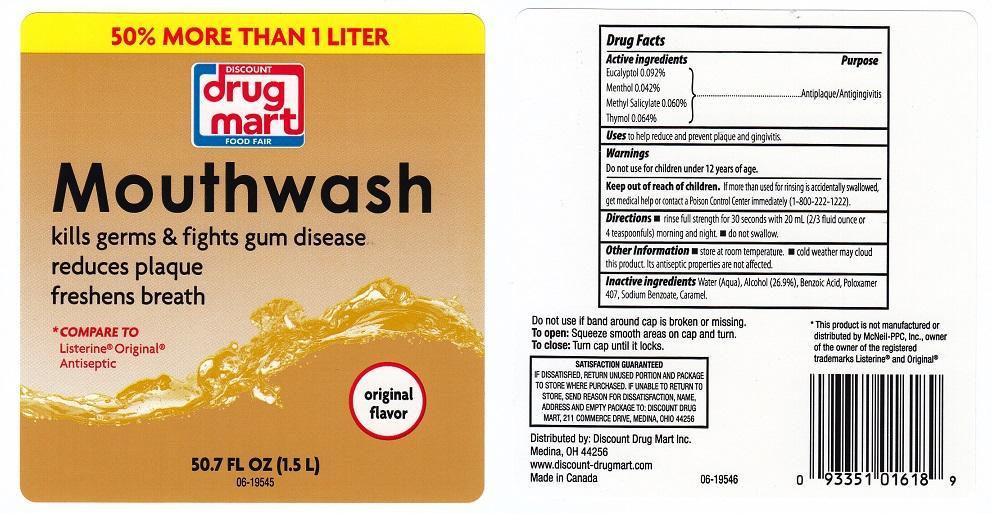 DRUG LABEL: DISCOUNT DRUG MART
NDC: 53943-556 | Form: LIQUID
Manufacturer: DISCOUNT DRUG MART
Category: otc | Type: HUMAN OTC DRUG LABEL
Date: 20241020

ACTIVE INGREDIENTS: EUCALYPTOL 0.92 mg/1 mL; MENTHOL 0.42 mg/1 mL; METHYL SALICYLATE 0.6 mg/1 mL; THYMOL 0.64 mg/1 mL
INACTIVE INGREDIENTS: WATER; ALCOHOL; BENZOIC ACID; POLOXAMER 407; SODIUM BENZOATE; CARAMEL

53943-556-51, Discount Drug Mart

ACTIVE INGREDIENTS

EUCALYPTOL 0.092%, MENTHOL 0.042%, METHYL SALICYLATE 0.060%, THYMOL 0.064%

PURPOSE

ANTIPLAQUE/ANTIGINGIVITIS

USES

TO HELP REDUCE AND PREVENT PLAQUE AND GINGIVITIS

WARNINGS

DO NOT USE FOR CHILDREN UNDER 12 YEARS OF AGE

KEEP OUT OF REACH OF CHILDREN

IF MORE THAN USED FOR RINSING IS ACCIDENTALLY SWALLOWED, GET MEDICAL HELP OR CONTACT A POISON CONTROL CENTER IMMEDIATELY (1-800-222-1222)

DIRECTIONS

RINSE FULL STRENGTH FOR 30 SECONDS WITH 20 ML (2/3 FLUID OUNCE OR 4 TEASPOONFULS) MORNING AND NIGHT. DO NOT SWALLOW

OTHER INFORMATION

STORE AT ROOM TEMPERATURE. COLD WEATHER MAY CLOUD THIS PRODUCT,ITS ANTISEPTIC PROPERTIES ARE NOT AFFECTED

INACTIVE INGREDIENTS

WATER (AQUA), ALCOHOL (26.9%), BENZOIC ACID, POLOXAMER 407, SODIUM BENZOATE, CARAMEL